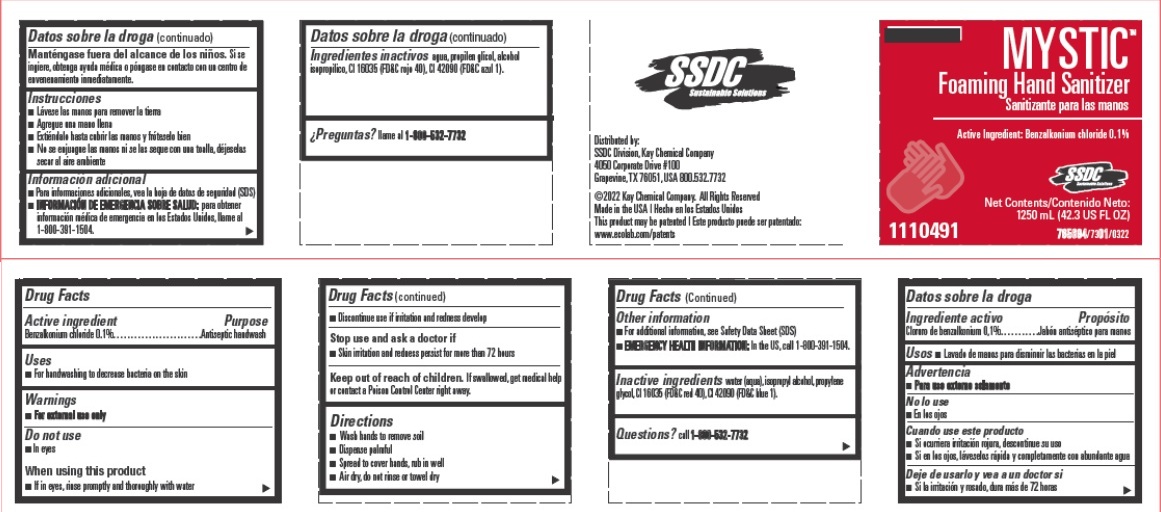 DRUG LABEL: SSDC Mystic Foaming Hand Sanitizer
NDC: 47593-674 | Form: SOLUTION
Manufacturer: Ecolab Inc.
Category: otc | Type: HUMAN OTC DRUG LABEL
Date: 20251217

ACTIVE INGREDIENTS: BENZALKONIUM CHLORIDE 1 mg/1 mL
INACTIVE INGREDIENTS: Water; Isopropyl alcohol; Propylene glycol; FD&C RED NO. 40; FD&C BLUE NO. 1

Drug Facts

Active ingredient

Benzalkonium chloride 0.1%

Purpose

Antiseptic handwash

Uses

- For handwashing to decrease bacteria on the skin

Warnings

- For external use only

Do not use

- In eyes

When using this product

- if in eyes, rinse promptly and thoroughly with water
- discontinue use if irritation and redness develop

Stop use and ask a doctor if

- skin irritation or redness occurs for more than 72 hours

Keep out of reach of children. If swallowed, get medical help or contact a Poison Control Center right away.

Directions

- wash hands to remove soil
- dispense palmful
- spread to cover hands, rub in well
- air dry, do not rinse or towel dry

Other information

- for additional information, see Safety Data Sheet (SDS)
- for emergency medical information in USA call 1-800-391-1504

INACTIVE INGREDIENT

Inactive ingredients water (aqua), isopropyl alcohol, propylene glycol, FD&C Red 40, FD&C Blue 1

Questions?

Call 1-800-532-7732

Principal display panel and representative container

SSDC

MYSTIC

Foaming Hand Sanitizer

Benzalkonium chloride 0.1%

Net Contents: 1250 mL/42.3 US fl oz

Distributed by: SSDC Division, Kay Chemical Company

4050 Corporate Drive, #100

Grapevine, Texas 76051, USA 800.532.7732